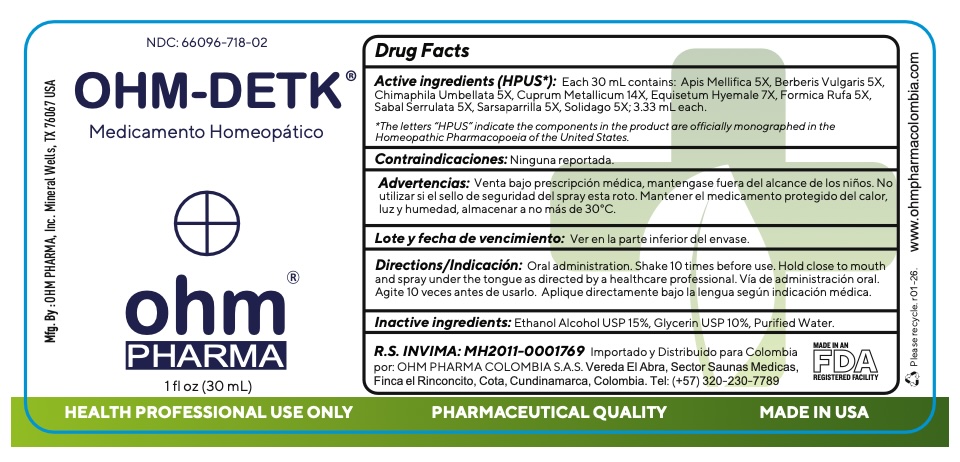 DRUG LABEL: OHM-DETK
NDC: 66096-718 | Form: SPRAY
Manufacturer: OHM PHARMA INC.
Category: homeopathic | Type: HUMAN OTC DRUG LABEL
Date: 20260128

ACTIVE INGREDIENTS: APIS MELLIFERA 5 [hp_X]/30 mL; BERBERIS VULGARIS ROOT BARK 5 [hp_X]/30 mL; CHIMAPHILA UMBELLATA WHOLE 5 [hp_X]/30 mL; COPPER 14 [hp_X]/30 mL; EQUISETUM HYEMALE WHOLE 7 [hp_X]/30 mL; FORMICA RUFA 5 [hp_X]/30 mL; SAW PALMETTO 5 [hp_X]/30 mL; SMILAX ORNATA ROOT 5 [hp_X]/30 mL; SOLIDAGO VIRGAUREA FLOWERING TOP 5 [hp_X]/30 mL
INACTIVE INGREDIENTS: ALCOHOL; GLYCERIN; WATER

OHM-DETK

ACTIVE INGREDIENT

Active ingredients (HPUS*):Each 100 mL contains: Apis Mellifica 5X, Berberis Vulgaris 5X,
Chimaphila Umbellata 5X, Cuprum Metallicum 14X, Equisetum Hyemale 7X, Formica Rufa 5X,
Sabal Serrulata 5X, Sarsaparrilla 5X, Solidago 5X; 3.30 mL each.

*The letters “HPUS” indicate the components in the product are officially monographed in the
Homeopathic Pharmacopoeia of the United States.

INDICATIONS AND USAGE

Contraindicaciones:Ninguna reportada.

WARNINGS

Advertencias:Venta bajo prescripción médica, mantengase fuera del alcance de los niños. No
utilizar si el sello de seguridad del spray esta roto. Mantener el medicamento protegido del calor,
luz y humedad, almacenar a no más de 30°C.

KEEP OUT OF REACH OF CHILDREN

Mantengase fuera del alcance de los niños.

DOSAGE AND ADMINISTRATION

Directions/Indicación:Oral administration. Shake 10 times before use. Hold close to mouth
and spray under the tongue as directed by a healthcare professional. Vía de administración oral.
Agite 10 veces antes de usarlo. Aplique directamente bajo la lengua según indicación médica.

INACTIVE INGREDIENT

Inactive ingredients:Ethanol Alcohol USP 15%, Glycerin USP 10%, Purified Water.

OTHER SAFETY INFORMATION

Lote y fecha de vencimiento:Ver en la parte inferior del envase.

QUESTIONS

R.S. INVIMA: MH2011-0001769

Importado y distribuido para Colombia por

OHM PHARMA COLOMBIA SAS

Vereda El Abra

Sector Saunas Medicas

Finca el Rinconcito

Cota, Cundinamarca, Colombia Tel: (+57) 320-230-7789

Mfg. By : OHM PHARMA, Inc.

Mineral Wells, TX 76067 USA
www.ohmpharma.com

PACKAGE LABEL

NDC: 66096-718-02

OHM-DETK

Medicamento Homeopático

ohm

PHARMA

1 fl oz (30 mL)

PURPOSE

Medicamento Homeopático